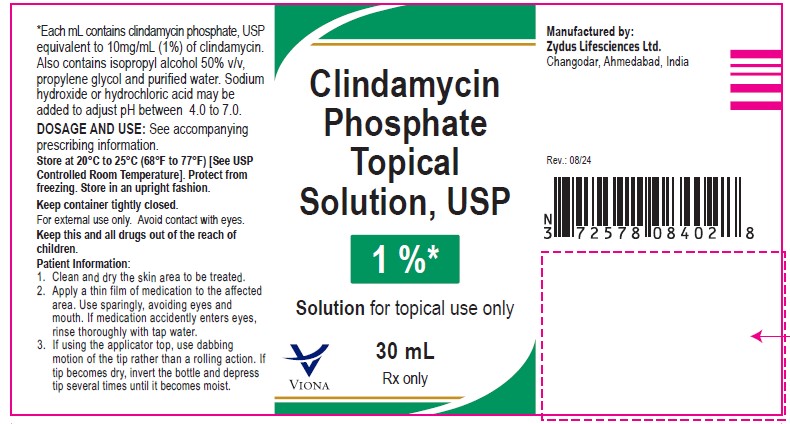 DRUG LABEL: Clindamycin phosphate
NDC: 70771-1414 | Form: SOLUTION
Manufacturer: Zydus Lifesciences Limited
Category: prescription | Type: HUMAN PRESCRIPTION DRUG LABEL
Date: 20240814

ACTIVE INGREDIENTS: CLINDAMYCIN PHOSPHATE 10 mg/1 mL
INACTIVE INGREDIENTS: HYDROCHLORIC ACID; ISOPROPYL ALCOHOL; PROPYLENE GLYCOL; SODIUM HYDROXIDE; WATER

Clindamycin Phosphate Topical Solution USP, 1%

PACKAGE LABEL.PRINCIPAL DISPLAY PANEL

NDC 70771-1414-2

Clindamycin phosphate topical solution USP, 1%

Rx only